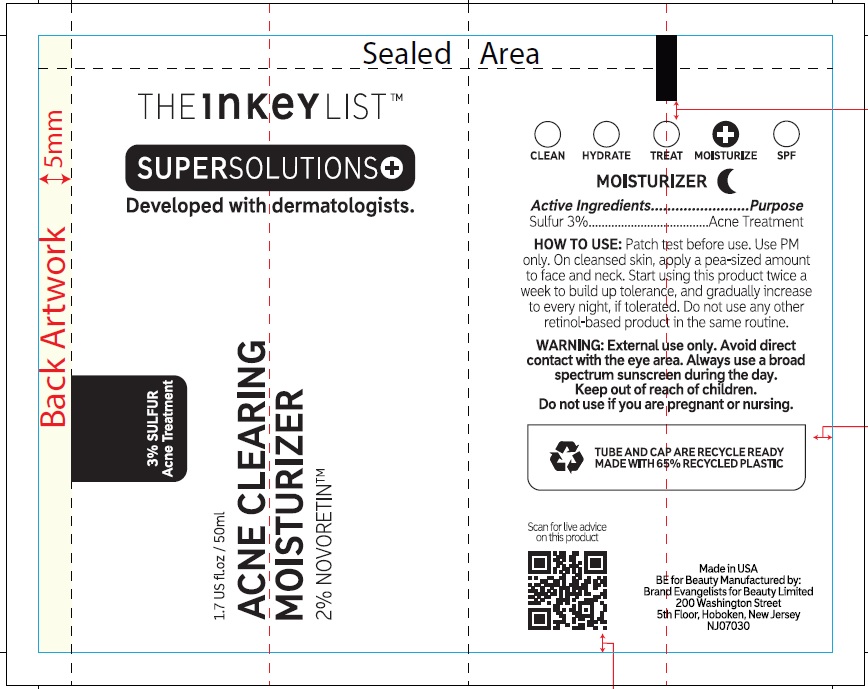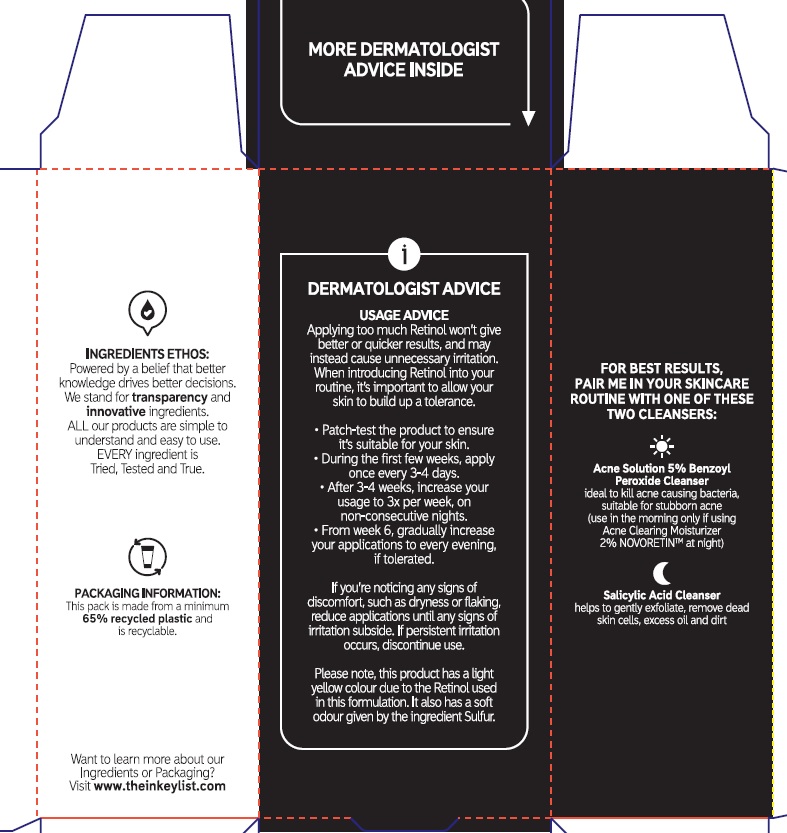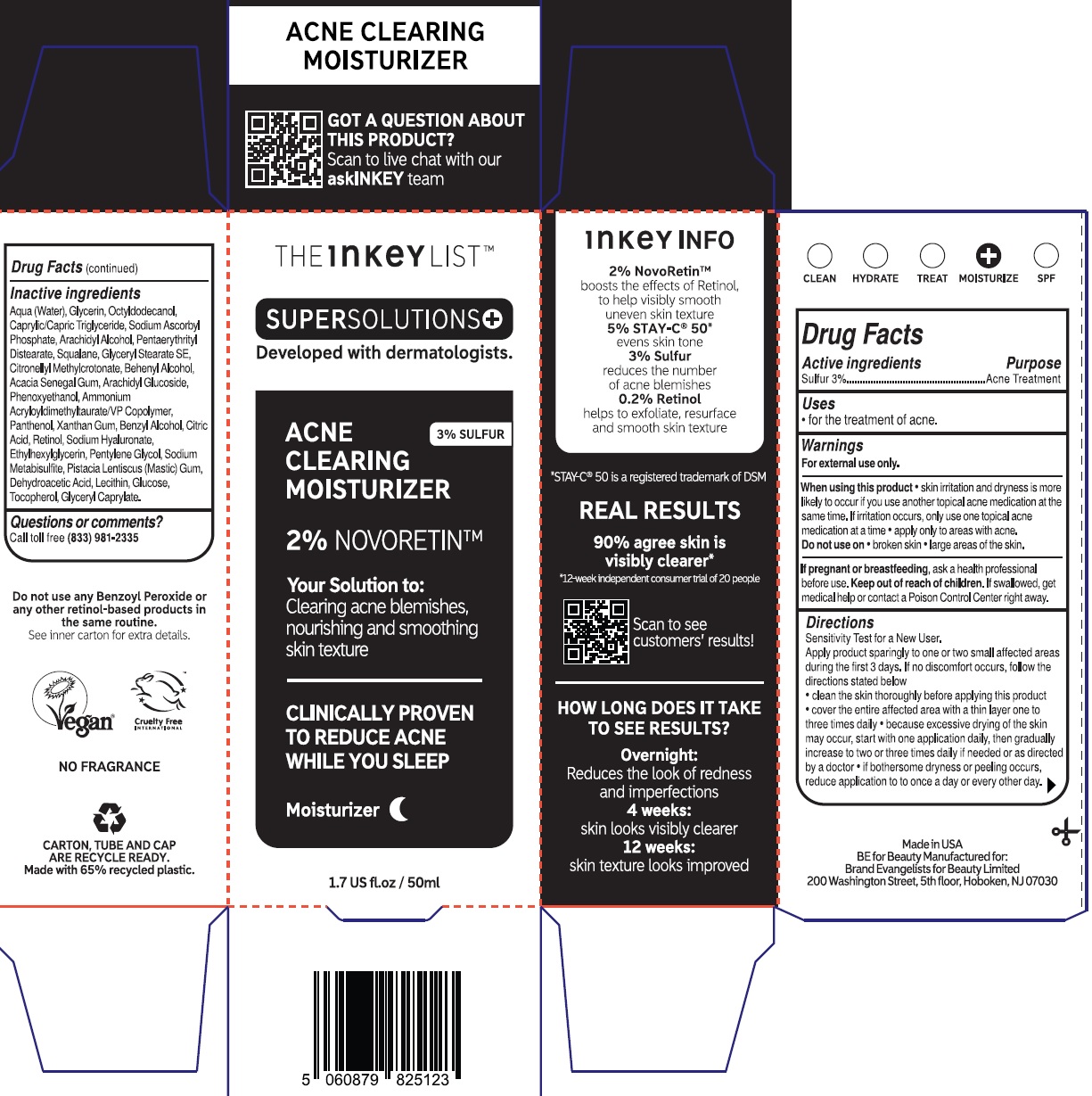 DRUG LABEL: The INKEY List Acne Clearing Moisturizer
NDC: 81136-024 | Form: CREAM
Manufacturer: Brand Evangelists for Beauty Limited
Category: otc | Type: HUMAN OTC DRUG LABEL
Date: 20231110

ACTIVE INGREDIENTS: SULFUR 30 mg/1 mL
INACTIVE INGREDIENTS: WATER; GLYCERIN; OCTYLDODECANOL; MEDIUM-CHAIN TRIGLYCERIDES; SODIUM ASCORBYL PHOSPHATE; ARACHIDYL ALCOHOL; PENTAERYTHRITYL DISTEARATE; SQUALANE; GLYCERYL STEARATE SE; CITRONELLYL METHYLCROTONATE; DOCOSANOL; ACACIA; ARACHIDYL GLUCOSIDE; PHENOXYETHANOL; AMMONIUM ACRYLOYLDIMETHYLTAURATE/VP COPOLYMER; PANTHENOL; XANTHAN GUM; BENZYL ALCOHOL; CITRIC ACID MONOHYDRATE; RETINOL; HYALURONATE SODIUM; ETHYLHEXYLGLYCERIN; PENTYLENE GLYCOL; SODIUM METABISULFITE; PISTACIA LENTISCUS RESIN; DEHYDROACETIC ACID; ANHYDROUS DEXTROSE; TOCOPHEROL; GLYCERYL MONOCAPRYLATE

The INKEY List Acne Clearing Moisturizer

Active ingredients

Sulfur 3%

Purpose

Acne Treatment

Uses

- for the treatment of acne.

Warnings

For external use only.

When using this product

- skin irritation and dryness is more likely to occur if you use another topical acne medication at the same time. If irritation occurs, only use one topical acne medication at a time
- apply only to areas with acne.

Do not use on

- broken skin
- large areas of the skin.

If pregnant or breastfeeding,

ask a health professional before use.

Keep out of reach of children.

If swallowed, get medical help or contact a Poison Control Cente right away.

Directions

Sensitivity Test for a New User.

Apply product sparingly to one or two small affected areas during the first 3 days. If no discomfort occurs, follow the directions stated below

- clean the skin thoroughly before applying this product
- cover the entire affected area with a thin layer one to three times daily
- because excessive drying of the skin may occurs, start with one application daily, then gradually increase to two or three times daily if needed or as directed by a doctor
- if bothersome dryness or peeling occurs, reduce application to to once a day or every other day.

Inactive ingredients

Aqua (Water), Glycerin, Octyldodecanol, Caprylic/Capric Triglyceride, Sodium Ascorbyl Phosphate, Arachidyl Alcohol, Pentaerythrityl Distearate, Squalane, Glyceryl Stearate SE, Citronellyl Methylcrotonate, Behenyl Alcohol, Acacia Senegal Gum, Arachidyl Glucoside, Phenoxyethanol, Ammonium Acryloyldimethyltaurate/VP Copolymer, Panthenol, Xanthan Gum, Benzyl Alcohol, Citric Acid, Retinol, Sodium Hyaluronate, Ethylhexylglycerin, Pentylene Glycol, Sodium Metabisulfite, Pistacia Lentiscus (Mastic) Gum, Dehydroacetic Acid, Lecithin, Glucose, Tocopherol, Glyceryl Caprylate.

Questions or comments?

Call toll free (833) 981-2335